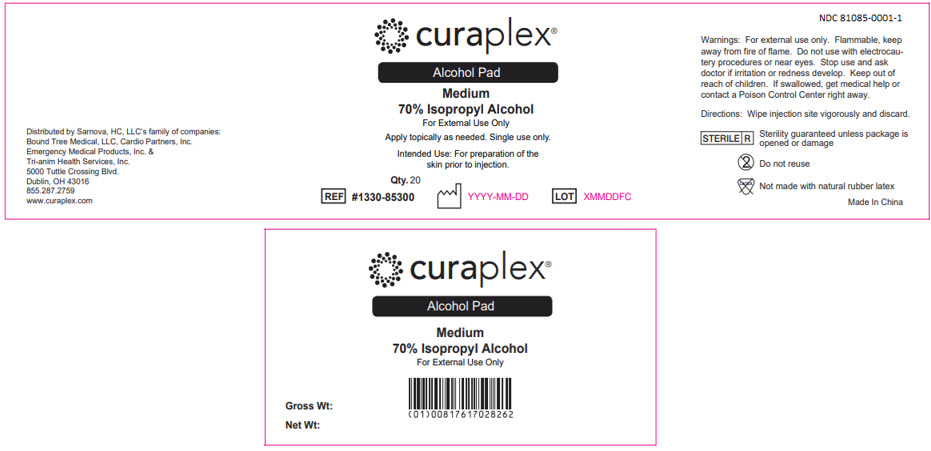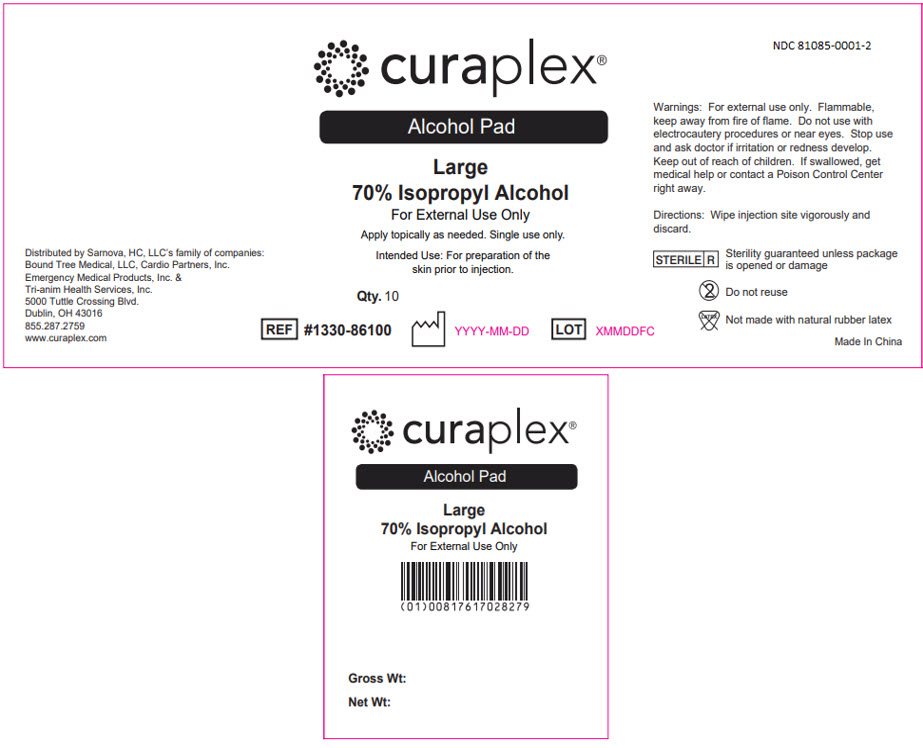 DRUG LABEL: Curaplex Alcohol Prep Pad
NDC: 81085-0001 | Form: SWAB
Manufacturer: Sarnova, Inc.
Category: otc | Type: HUMAN OTC DRUG LABEL
Date: 20241212

ACTIVE INGREDIENTS: ISOPROPYL ALCOHOL 0.7 mL/1 mL
INACTIVE INGREDIENTS: WATER

Drug Facts

Active ingredient:

Isopropyl Alcohol 70%

Purpose:

Antiseptic Cleanser

Use

For preparation of the skin prior to an injection.

Warnings:

For external use only.

Do not use:

- with electrocautery procedures ν
- in the eyes. If contact occurs, flush eyes with water.

Flammable, keep away from fire or flame.

Stop use and ask a doctor if irritation and redness develop

Keep out of reach of children. If swallowed, get medical help. or contact a Poison Control Center right away.

Directions

Wipe injection site vigorously and discard.

Other Information

Store at room temperature.

Inactive ingredients

purified water

Questions?

855-287-2759

Principal Display Panel - 0.4 mL Pouch Box Case Label

Distributed by Sarnova, HC, LLC's family of companies:
Bound Tree Medical, LLC, Cardio Partners, Inc.
Emergency Medical Products, Inc. &
Tri-anim Health Services, Inc.
5000 Tuttle Crossing Blvd.
Dublin, OH 43016
855.287.2759
www.curaplex.com

curaplex®

Alcohol Pad

Medium
70% Isopropyl Alcohol
For External Use Only

Apply topically as needed. Single use only.

Intended Use: For preparation of the
skin prior to injection.

Qty. 20

REF #1330-85300
YYYY-MM-DD
LOT
XMMDDFC

NDC 81085-0001-1

Warnings: For external use only. Flammable, keep
away from fire of flame. Do not use with electrocau-
tery procedures or near eyes. Stop use and ask
doctor if irritation or redness develop. Keep out of
reach of children. If swallowed, get medical help or
contact a Poison Control Center right away.

Directions: Wipe injection site vigorously and discard.

STERILE R

Sterility guaranteed unless package is
opened or damage

Do not reuse

Not made with natural rubber latex

Made in China

Principal Display Panel - 0.8 mL Pouch Box Case Label

Distributed by Sarnova, HC, LLC's family of companies:
Bound Tree Medical, LLC, Cardio Partners, Inc.
Emergency Medical Products, Inc. &
Tri-anim Health Services, Inc.
5000 Tuttle Crossing Blvd.
Dublin, OH 43016
855.287.2759
www.curaplex.com

curaplex®

Alcohol Pad

Large
70% Isopropyl Alcohol
For External Use Only

Apply topically as needed. Single use only.

Intended Use: For preparation of the
skin prior to injection.

Qty. 10

REF #1330-86100
YYYY-MM-DD
LOT
XMMDDFC

NDC 81085-0001-2

Warnings: For external use only. Flammable,
keep away from fire of flame. Do not use with
electrocautery procedures or near eyes. Stop use
and ask doctor if irritation or redness develop.
Keep out of reach of children. If swallowed, get
medical help or contact a Poison Control Center
right away.

Directions: Wipe injection site vigorously and
discard.

STERILE R

Sterility guaranteed unless package
is opened or damage

Do not reuse

Not made with natural rubber latex

Made in China